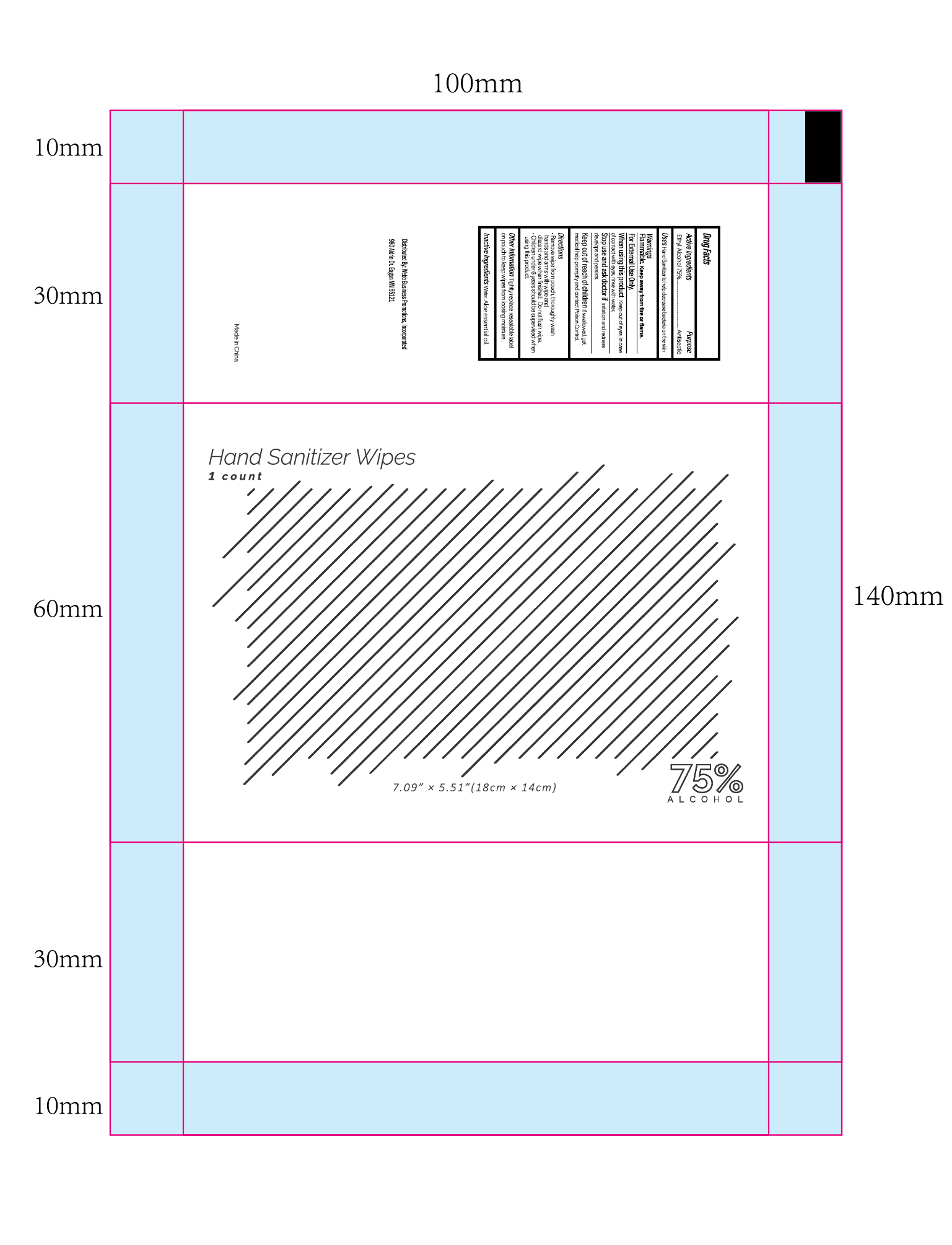 DRUG LABEL: Antibacterial Hand Sanitizer
NDC: 70445-417 | Form: SWAB
Manufacturer: Webb Business Promotions, Inc
Category: otc | Type: HUMAN OTC DRUG LABEL
Date: 20220104

ACTIVE INGREDIENTS: ALCOHOL 75 mL/100 mL
INACTIVE INGREDIENTS: ALOE VERA LEAF; WATER

Antibacterial Hand Sanitizer

Active Ingridient

Ethyl Alcohol 75%

PURPOSE

Antiseptic

When using this product Keep out of eyes. In case of contact with eyes, rinse with water.

WARNINGS

Flammable. Keep away from fire or flame.

For External Use Only.

When using this product Keep out of eyes. In case of contact with eyes,rinse with water.

Stop use and ask doctor if irritation and redness develops and persists.

Keep out of reach of children If swallowed, get medical help promptly and contact Poison Control.

Stop use and ask doctor if irritation and redness develops and persists

Keep out of reach of children If swallowed, get medical help promptly and contact Poison Control.

OTHER SAFETY INFORMATION

Tightly replace resealable label on pouch to keep wipes from loosing moisture.

INACTIVE INGREDIENT

Water, Aloe essential oil

INDICATIONS AND USAGE

Hand Sanitizer to help decrease bacteria on the skin

DOSAGE AND ADMINISTRATION

Remove wipe from pouch, thoroughly wash hands and arms with wipe and discard wipe when finished. Do not flush wipe.
Children under 6 years should be supervised when using this product.